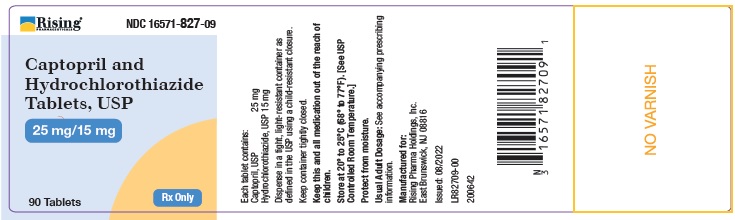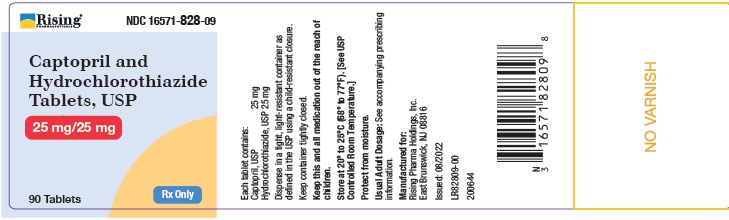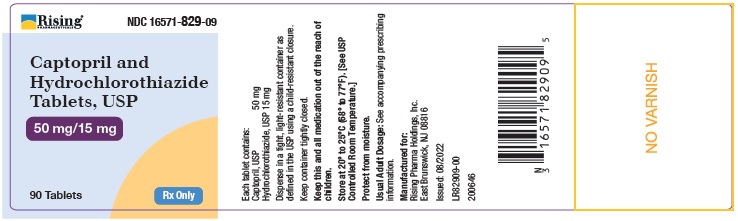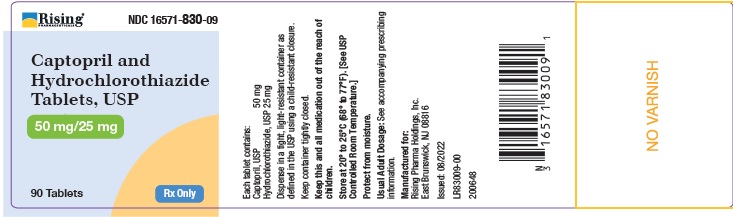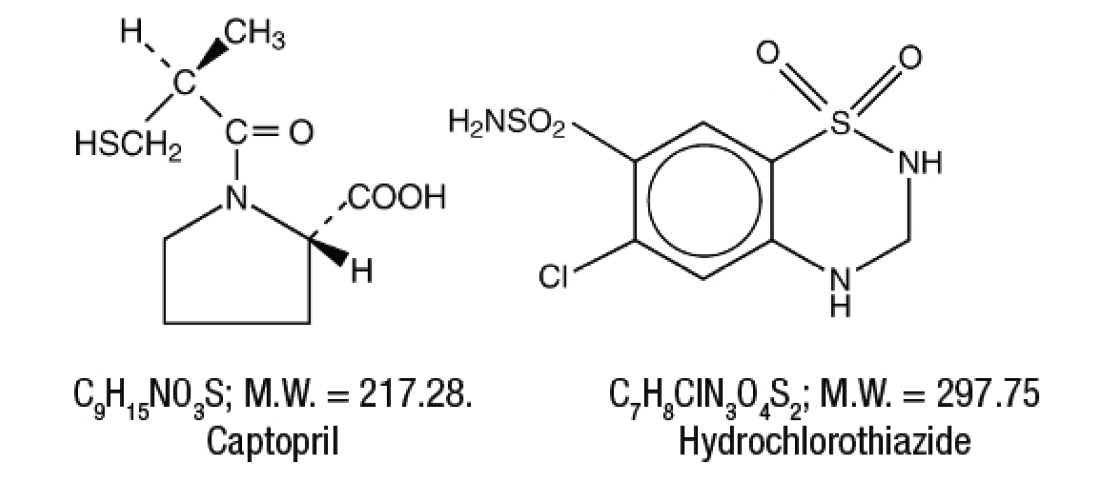 DRUG LABEL: CAPTOPRIL AND HYDROCHLOROTHIAZIDE
NDC: 16571-827 | Form: TABLET
Manufacturer: Rising Pharma Holdings, Inc.
Category: prescription | Type: Human Prescription Drug Label
Date: 20230221

ACTIVE INGREDIENTS: CAPTOPRIL 25 mg/1 1; HYDROCHLOROTHIAZIDE 15 mg/1 1
INACTIVE INGREDIENTS: ANHYDROUS LACTOSE; SILICON DIOXIDE; CROSCARMELLOSE SODIUM; MAGNESIUM STEARATE; CELLULOSE, MICROCRYSTALLINE; STARCH, CORN; SODIUM LAURYL SULFATE

BOXED WARNING

USE IN PREGNANCY
When used in pregnancy during the second and third trimesters, ACE Inhibitors can cause injury and even death to the developing fetus. When pregnancy is detected, captopril and hydrochlorothiazide should be discontinued as soon as possible. See WARNINGS: Captopril: Fetal/Neonatal Morbidity and Mortality.

DESCRIPTION

Captopril and hydrochlorothiazide tablets, USP for oral administration combines two antihypertensive agents: captopril and hydrochlorothiazide. Captopril, the first of a new class of antihypertensive agents, is a specific competitive inhibitor of angiotensin I-converting enzyme (ACE), the enzyme responsible for the conversion of angiotensin I to angiotensin II. Hydrochlorothiazide is a benzothiadiazide (thiazide) diuretic-antihypertensive.
Captopril, USP is a white to off-white crystalline powder with characteristic sulfide-like odor; it is freely soluble in water, ethanol, methanol, chloroform, isopropyl alcohol and methylene chloride and soluble in ethyl acetate. It dissolves in dilute solution of alkali hydroxide.
Hydrochlorothiazide, USP is a white or almost white, almost odorless crystalline powder. Very slightly soluble in water, sparingly soluble in Ethanol and Methanol, soluble in Acetone. Freely soluble in N,N-Dimethylformamide, in n-Butylamine and in diluted solutions of alkali hydroxides. Practically insoluble in Ether, in Chloroform and in diluted mineral acids.
Captopril is designated chemically as 1-[(2S)-3-Mercapto-2-methylpropionyl]-L-proline; Hydrochlorothiazide is 6-Chloro-3,4-dihydro-2H-1,2,4-benzothiadiazine-7-sulfonamide 1,1-dioxide. Their structural formulas are:

Captopril and hydrochlorothiazide tablets are available for oral administration in four combinations of captopril with hydrochlorothiazide: 25 mg with 15 mg, 25 mg with 25 mg, 50 mg with 15 mg, and 50 mg with 25 mg. In addition, each tablet contains the following inactive ingredients: anhydrous lactose, colloidal silicon dioxide, croscarmellose sodium, magnesium stearate, microcrystalline cellulose, pregelatinized starch (corn) and sodium lauryl sulfate. The 25 mg/25 mg and 50 mg/25 mg tablets also contain FD&C Yellow No. 6 Aluminum Lake.

CLINICAL PHARMACOLOGY

Captopril: Mechanism of Action: The mechanism of action of captopril has not yet been fully elucidated. Its beneficial effects in hypertension and heart failure appear to result primarily from suppression of the renin-angiotensin-aldosterone system. However, there is no consistent correlation between renin levels and response to the drug. Renin, an enzyme synthesized by the kidneys, is released into the circulation where it acts on a plasma globulin substrate to produce angiotensin I, a relatively inactive decapeptide. Angiotensin I is then converted by angiotensin converting enzyme (ACE) to angiotensin II, a potent endogenous vasoconstrictor substance. Angiotensin II also stimulates aldosterone secretion from the adrenal cortex, thereby contributing to sodium and fluid retention.
Captopril prevents the conversion of angiotensin I to angiotensin II by inhibition of ACE, a peptidyldipeptide carboxy hydrolase. This inhibition has been demonstrated in both healthy human subjects and in animals by showing that the elevation of blood pressure caused by exogenously administered angiotensin I was attenuated or abolished by captopril. In animal studies, captopril did not alter the pressor responses to a number of other agents, including angiotensin II and norepinephrine, indicating specificity of action.

ACE is identical to “bradykininase”, and captopril may also interfere with the degradation of the vasodepressor peptide, bradykinin. Increased concentrations of bradykinin or prostaglandin E2 may also have a role in the therapeutic effect of captopril.

Inhibition of ACE results in decreased plasma angiotensin II and increased plasma renin activity (PRA), the latter resulting from loss of negative feedback on renin release caused by reduction in angiotensin II. The reduction of angiotensin II leads to decreased aldosterone secretion, and, as a result, small increases in serum potassium may occur along with sodium and fluid loss.

The antihypertensive effects persist for a longer period of time than does demonstrable inhibition of circulating ACE. It is not known whether the ACE present in vascular endothelium is inhibited longer than the ACE in circulating blood.

Pharmacokinetics:

After oral administration of therapeutic doses of captopril, rapid absorption occurs with peak blood levels at about one hour. The presence of food in the gastrointestinal tract reduces absorption by about 30 to 40 percent; captopril therefore should be given one hour before meals. Based on carbon-14 labeling, average minimal absorption is approximately 75 percent. In a 24-hour period, over 95 percent of the absorbed dose is eliminated in the urine; 40 to 50 percent is unchanged drug; most of the remainder is the disulfide dimer of captopril and captopril-cysteine disulfide.
Approximately 25 to 30 percent of the circulating drug is bound to plasma proteins. The apparent elimination half-life for total radioactivity in blood is probably less than three hours. An accurate determination of half-life of unchanged captopril is not, at present, possible, but it is probably less than two hours. In patients with renal impairment, however, retention of captopril occurs (see DOSAGE AND ADMINISTRATION).

Pharmacodynamics:

Administration of captopril results in a reduction of peripheral arterial resistance in hypertensive patients with either no change, or an increase, in cardiac output. There is an increase in renal blood flow following administration of captopril and glomerular filtration rate is usually unchanged. In patients with heart failure, significantly decreased peripheral (systemic vascular) resistance and blood pressure (afterload), reduced pulmonary capillary wedge pressure (preload) and pulmonary vascular resistance, increased cardiac output, and increased exercise tolerance time (ETT) have been demonstrated.

Reductions of blood pressure are usually maximal 60 to 90 minutes after oral administration of an individual dose of captopril. The duration of effect is dose related and is extended in the presence of a thiazide-type diuretic. The full effect of a given dose may not be attained for 6 to 8 weeks (see DOSAGE AND ADMINISTRATION). The blood pressure lowering effects of captopril and thiazide-type diuretics are additive. In contrast, captopril and beta-blockers have a less than additive effect.

Blood pressure is lowered to about the same extent in both standing and supine positions. Orthostatic effects and tachycardia are infrequent but may occur in volume-depleted patients. Abrupt withdrawal of captopril has not been associated with a rapid increase in blood pressure.
Studies in rats and cats indicate that captopril does not cross the blood-brain barrier to any significant extent.
Hydrochlorothiazide: Thiazides affect the renal tubular mechanism of electrolyte reabsorption. At maximal therapeutic dosage all thiazides are approximately equal in their diuretic potency.
Thiazides increase excretion of sodium and chloride in approximately equivalent amounts. Natriuresis causes a secondary loss of potassium and bicarbonate.
The mechanism of the antihypertensive effect of thiazides is unknown. Thiazides do not affect normal blood pressure.
The mean plasma half-life of hydrochlorothiazide in fasted individuals has been reported to be approximately 2.5 hours.
Onset of diuresis occurs in two hours and the peak effect at about four hours. Its action persists for approximately six to twelve hours. Hydrochlorothiazide is eliminated rapidly by the kidney.

INDICATIONS & USAGE

Captopril and hydrochlorothiazide tablets are indicated for the treatment of hypertension. The blood pressure lowering effects of captopril and thiazides are approximately additive.
This fixed combination drug may be used as initial therapy or substituted for previously titrated doses of the individual components.
When captopril and hydrochlorothiazide are given together it may not be necessary to administer captopril in divided doses to attain blood pressure control at trough (before the next dose). Also, with such a combination, a daily dose of 15 mg of hydrochlorothiazide may be adequate.
Treatment may, therefore, be initiated with captopril and hydrochlorothiazide tablets 25 mg/15 mg once daily. Subsequent titration should be with additional doses of the components (captopril, hydrochlorothiazide) as single agents or as captopril and hydrochlorothiazide tablets 50 mg/15 mg, 25 mg/25 mg, or 50 mg/25 mg (see DOSAGE AND ADMINISTRATION).

In using captopril and hydrochlorothiazide, consideration should be given to the risk of neutropenia/agranulocytosis (see WARNINGS).

Captopril and hydrochlorothiazide may be used for patients with normal renal function, in whom the risk is relatively low. In patients with impaired renal function, particularly those with collagen vascular disease, captopril and hydrochlorothiazide should be reserved for hypertensives who have either developed unacceptable side effects on other drugs, or have failed to respond satisfactorily to other drug combinations.

ACE inhibitors (for which adequate data are available) cause a higher rate of angioedema in black than in non-black patients (see WARNINGS: Captopril: Head and Neck Angioedema and Intestinal Angioedema).

CONTRAINDICATIONS

Captopril: This product is contraindicated in patients who are hypersensitive to captopril or any other angiotensin-converting enzyme inhibitor (e.g., a patient who has experienced angioedema during therapy with any other ACE inhibitor).
Hydrochlorothiazide: Hydrochlorothiazide is contraindicated in anuria. It is also contraindicated in patients who have previously demonstrated hypersensitivity to hydrochlorothiazide or other sulfonamide-derived drugs.

WARNINGS

Captopril: Anaphylactoid and Possible Related Reactions: Presumably because angiotensin-converting enzyme inhibitors affect the metabolism of eicosanoids and polypeptides, including endogenous bradykinin, patients receiving ACE inhibitors (including captopril) may be subject to a variety of adverse reactions, some of them serious.

Head and Neck Angioedema: Angioedema involving the extremities, face, lips, mucous membranes, tongue, glottis or larynx has been seen in patients treated with ACE inhibitors, including captopril. If angioedema involves the tongue, glottis or larynx, airway obstruction may occur and be fatal. Emergency therapy, including but not necessarily limited to, subcutaneous administration of a 1:1000 solution of epinephrine should be promptly instituted.

Swelling confined to the face, mucous membranes of the mouth, lips and extremities has usually resolved with discontinuation of treatment; some cases required medical therapy. (See PRECAUTIONS: Information for Patients and ADVERSE REACTIONS: Captopril.)

Intestinal Angioedema: Intestinal angioedema has been reported in patients treated with ACE inhibitors. These patients presented with abdominal pain (with or without nausea or vomiting); in some cases there was no prior history of facial angioedema and C-1 esterase levels were normal. The angioedema was diagnosed by procedures including abdominal CT scan or ultrasound, or at surgery, and symptoms resolved after stopping the ACE inhibitor. Intestinal angioedema should be included in the differential diagnosis of patients on ACE inhibitors presenting with abdominal pain.

Anaphylactoid Reactions During Desensitization: Two patients undergoing desensitizing treatment with hymenoptera venom while receiving ACE inhibitors sustained life-threatening anaphylactoid reactions. In the same patients, these reactions were avoided when ACE inhibitors were temporarily withheld, but they reappeared upon inadvertent rechallenge.
Anaphylactoid Reactions During Membrane Exposure: Anaphylactoid reactions have been reported in patients dialyzed with high-flux membranes and treated concomitantly with an ACE inhibitor. Anaphylactoid reactions have also been reported in patients undergoing low-density lipoprotein apheresis with dextran sulfate absorption.
Neutropenia/Agranulocytosis: Neutropenia (< 1000/mm^3) with myeloid hypoplasia has resulted from use of captopril. About half of the neutropenic patients developed systemic or oral cavity infections or other features of the syndrome of agranulocytosis.
The risk of neutropenia is dependent on the clinical status of the patient:
In clinical trials in patients with hypertension who have normal renal function (serum creatinine less than 1.6 mg/dL and no collagen vascular disease), neutropenia has been seen in one patient out of over 8,600 exposed.
In patients with some degree of renal failure (serum creatinine at least 1.6 mg/dL) but no collagen vascular disease, the risk of neutropenia in clinical trials was about 1 per 500, a frequency over 15 times that for uncomplicated hypertension. Daily doses of captopril were relatively high in these patients, particularly in view of their diminished renal function. In foreign marketing experience in patients with renal failure, use of allopurinol concomitantly with captopril has been associated with neutropenia but this association has not appeared in U.S. reports.
In patients with collagen vascular diseases (e.g., systemic lupus erythematosus, scleroderma) and impaired renal function, neutropenia occurred in 3.7 percent of patients in clinical trials.
While none of the over 750 patients in formal clinical trials of heart failure developed neutropenia, it has occurred during the subsequent clinical experience. About half of the reported cases had serum creatinine ≥ 1.6 mg/dL and more than 75 percent were in patients also receiving procainamide. In heart failure, it appears that the same risk factors for neutropenia are present.
The neutropenia has usually been detected within three months after captopril was started. Bone marrow examinations in patients with neutropenia consistently showed myeloid hypoplasia, frequently accompanied by erythroid hypoplasia and decreased numbers of megakaryocytes (e.g., hypoplastic bone marrow and pancytopenia); anemia and thrombocytopenia were sometimes seen.
In general, neutrophils returned to normal in about two weeks after captopril was discontinued, and serious infections were limited to clinically complex patients. About 13 percent of the cases of neutropenia have ended fatally, but almost all fatalities were in patients with serious illness, having collagen vascular disease, renal failure, heart failure or immunosuppressant therapy, or a combination of these complicating factors.

Evaluation of the hypertensive or heart failure patient should always include assessment of renal function.
If captopril is used in patients with impaired renal function, white blood cell and differential counts should be evaluated prior to starting treatment and at approximately two-week intervals for about three months, then periodically.
In patients with collagen vascular disease or who are exposed to other drugs known to affect the white cells or immune response, particularly when there is impaired renal function, captopril should be used only after an assessment of benefit and risk, and then with caution.
All patients treated with captopril should be told to report any signs of infection (e.g., sore throat, fever). If infection is suspected, white cell counts should be performed without delay.
Since discontinuation of captopril and other drugs has generally led to prompt return of the white count to normal, upon confirmation of neutropenia (neutrophil count < 1000/mm^3) the physician should withdraw captopril and closely follow the patient’s course.
Proteinuria: Total urinary proteins greater than 1 g per day were seen in about 0.7 percent of patients receiving captopril. About 90 percent of affected patients had evidence of prior renal disease or received relatively high doses of captopril (in excess of 150 mg/day), or both. The nephrotic syndrome occurred in about one-fifth of proteinuric patients. In most cases, proteinuria subsided or cleared within six months whether or not captopril was continued. Parameters of renal function, such as BUN and creatinine, were seldom altered in the patients with proteinuria.
Hypotension: Excessive hypotension was rarely seen in hypertensive patients but is a possible consequence of captopril use in salt/volume depleted persons (such as those treated vigorously with diuretics), patients with heart failure or those patients undergoing renal dialysis. (See PRECAUTIONS: Drug Interactions.)
Fetal/Neonatal Morbidity and Mortality: ACE inhibitors can cause fetal and neonatal morbidity and death when administered to pregnant women. Several dozen cases have been reported in the world literature. When pregnancy is detected, ACE inhibitors should be discontinued as soon as possible.
The use of ACE inhibitors during the second and third trimesters of pregnancy has been associated with fetal and neonatal injury, including hypotension, neonatal skull hypoplasia, anuria, reversible or irreversible renal failure, and death. Oligohydramnios has also been reported, presumably resulting from decreased fetal renal function; oligohydramnios in this setting has been associated with fetal limb contractures, craniofacial deformation, and hypoplastic lung development. Prematurity, intrauterine growth retardation, and patent ductus arteriosus have also been reported, although it is not clear whether these occurrences were due to the ACE-inhibitor exposure.
These adverse effects do not appear to have resulted from intrauterine ACE-inhibitor exposure that has been limited to the first trimester. Mothers whose embryos and fetuses are exposed to ACE inhibitors only during the first trimester should be so informed. Nonetheless, when patients become pregnant, physicians should make every effort to discontinue the use of captopril as soon as possible.

Rarely (probably less often than once in every thousand pregnancies), no alternative to ACE inhibitors will be found. In these rare cases, the mothers should be apprised of the potential hazards to their fetuses, and serial ultrasound examinations should be performed to assess the intraamniotic environment.

If oligohydramnios is observed, captopril should be discontinued unless it is considered life-saving for the mother. Contraction stress testing (CST), a non-stress test (NST), or biophysical profiling (BPP) may be appropriate, depending upon the week of pregnancy. Patients and physicians should be aware, however, that oligohydramnios may not appear until after the fetus has sustained irreversible injury.
Infants with histories of in utero exposure to ACE inhibitors should be closely observed for hypotension, oliguria, and hyperkalemia. If oliguria occurs, attention should be directed toward support of blood pressure and renal perfusion. Exchange transfusion or dialysis may be required as a means of reversing hypotension and/or substituting for disordered renal function. While captopril may be removed from the adult circulation by hemodialysis, there is inadequate data concerning the effectiveness of hemodialysis for removing it from the circulation of neonates or children. Peritoneal dialysis is not effective for removing captopril; there is no information concerning exchange transfusion for removing captopril from the general circulation.
When captopril was given to rabbits at doses about 0.8 to 70 times (on a mg/kg basis) the maximum recommended human dose, low incidences of craniofacial malformations were seen. No teratogenic effects of captopril were seen in studies of pregnant rats and hamsters. On a mg/kg basis, the doses used were up to 150 times (in hamsters) and 625 times (in rats) the maximum recommended human dose.
Hepatic Failure: Rarely, ACE Inhibitors have been associated with a syndrome that starts with cholestatic jaundice and progresses to fulminant hepatic necrosis and (sometimes) death. The mechanism of this syndrome is not understood. Patients receiving ACE inhibitors who develop jaundice or marked elevations of hepatic enzymes should discontinue the ACE inhibitor and receive appropriate medical follow-up.
Hydrochlorothiazide: Thiazides should be used with caution in severe renal disease. In patients with renal disease, thiazides may precipitate azotemia. Cumulative effects of the drug may develop in patients with impaired renal function.
Thiazides should be used with caution in patients with impaired hepatic function or progressive liver disease, since minor alterations of fluid and electrolyte balance may precipitate hepatic coma.
Sensitivity reactions may occur in patients with or without a history of allergy or bronchial asthma.
The possibility of exacerbation or activation of systemic lupus erythematosus has been reported.
In general, lithium should not be given with diuretics (see PRECAUTIONS: Drug Interactions: Hydrochlorothiazide).

PRECAUTIONS

GENERAL PRECAUTIONS

General: Captopril: Impaired Renal Function: Some patients with renal disease, particularly those with severe renal artery stenosis, have developed increases in BUN and serum creatinine after reduction of blood pressure with captopril. Captopril dosage reduction and/or discontinuation of diuretic may be required. For some of these patients, it may not be possible to normalize blood pressure and maintain adequate renal perfusion (see CLINICAL PHARMACOLOGY, DOSAGE AND ADMINISTRATION, ADVERSE REACTIONS: Altered Laboratory Findings).
Hyperkalemia: Elevations in serum potassium have been observed in some patients treated with ACE inhibitors, including captopril. When treated with ACE inhibitors, patients at risk for the development of hyperkalemia include those with: renal insufficiency; diabetes mellitus; and those using concomitant potassium-sparing diuretics, potassium supplements or potassium-containing salt substitutes; or other drugs associated with increases in serum potassium. (See PRECAUTIONS: Information for Patients and Drug Interactions: Captopril; ADVERSE REACTIONS: Altered Laboratory Findings.)
Cough: Presumably due to the inhibition of the degradation of endogenous bradykinin, persistent nonproductive cough has been reported with all ACE inhibitors, always resolving after discontinuation of therapy. ACE inhibitor-induced cough should be considered in the differential diagnosis of cough.
Surgery/Anesthesia: In patients undergoing major surgery or during anesthesia with agents that produce hypotension, captopril will block angiotensin II formation secondary to compensatory renin release. If hypotension occurs and is considered to be due to this mechanism, it can be corrected by volume expansion.
Hemodialysis: Recent clinical observations have shown an association of hypersensitivity-like (anaphylactoid) reactions during hemodialysis with high-flux dialysis membranes (e.g., AN69) in patients receiving ACE inhibitors as medication. In these patients, consideration should be given to using a different type of dialysis membrane or a different class of medication. (See WARNINGS: Captopril: Anaphylactoid Reactions During Membrane Exposure).
Hydrochlorothiazide: Periodic determination of serum electrolytes to detect possible electrolyte imbalance should be performed at appropriate intervals.
All patients receiving thiazide therapy should be observed for clinical signs of fluid or electrolyte imbalance, namely: hyponatremia, hypochloremic alkalosis, and hypokalemia. Serum and urine electrolyte determinations are particularly important when the patient is vomiting excessively or receiving parenteral fluids. Warning signs or symptoms of fluid and electrolyte imbalance may include: dryness of mouth, thirst, weakness, lethargy, drowsiness, restlessness, muscle pains or cramps, muscular fatigue, hypotension, oliguria, tachycardia, and gastrointestinal disturbances such as nausea and vomiting.
Hypokalemia may develop, especially with brisk diuresis, or when severe cirrhosis is present. Interference with adequate oral electrolyte intake will also contribute to hypokalemia. Hypokalemia can sensitize or exaggerate the response of the heart to the toxic effects of digitalis (e.g., increased ventricular irritability). Because captopril reduces the production of aldosterone, concomitant therapy with captopril reduces the diuretic-induced hypokalemia. Fewer patients may require potassium supplements and/or foods with a high potassium content (see Drug Interactions: Captopril: Agents Increasing Serum Potassium).
Any chloride deficit is generally mild and usually does not require specific treatment except under extraordinary circumstances (as in liver disease or renal disease). Dilutional hyponatremia may occur in edematous patients in hot weather; appropriate therapy is water restriction, rather than administration of salt except in rare instances when the hyponatremia is life-threatening. In actual salt depletion, appropriate replacement is the therapy of choice.
Hyperuricemia may occur or frank gout may be precipitated in certain patients receiving thiazide therapy.
Latent diabetes mellitus may become manifest during thiazide administration.
The antihypertensive effect of thiazide diuretics may be enhanced in the postsympathectomy patient.
If progressive renal impairment becomes evident, as indicated by a rising nonprotein nitrogen or blood urea nitrogen (BUN), a careful reappraisal of therapy is necessary with consideration given to withholding or discontinuing diuretic therapy.
Thiazides may decrease serum PBI levels without signs of thyroid disturbance.
Calcium excretion is decreased by thiazides. Pathological changes in the parathyroid gland with hypercalcemia and hypophosphatemia have been observed in a few patients on prolonged thiazide therapy. The common complications of hyperparathyroidism such as renal lithiasis, bone resorption, and peptic ulceration have not been seen. Thiazides should be discontinued before carrying out tests for parathyroid function.
Thiazides have been shown to increase the urinary excretion of magnesium; this may result in hypomagnesemia.

INFORMATION FOR PATIENTS

Patients should be advised to immediately report to their physician any signs or symptoms suggesting angioedema (e.g., swelling of face, eyes, lips, tongue, larynx and extremities; difficulty in swallowing or breathing; hoarseness) and to discontinue therapy. (See WARNINGS: Captopril: Head and Neck Angioedema and Intestinal Angioedema.)
Patients should be told to report promptly any indication of infection (e.g., sore throat, fever), which may be a sign of neutropenia, or of progressive edema which might be related to proteinuria and nephrotic syndrome.
All patients should be cautioned that excessive perspiration and dehydration may lead to an excessive fall in blood pressure because of reduction in fluid volume. Other causes of volume depletion such as vomiting or diarrhea may also lead to a fall in blood pressure; patients should be advised to consult with the physician.
Patients should be advised not to use potassium-sparing diuretics, potassium supplements or potassium-containing salt substitutes without consulting their physician. (See PRECAUTIONS: General and Drug Interactions: Captopril ; ADVERSE REACTIONS: Captopril.)
Patients should be warned against interruption or discontinuation of medication unless instructed by the physician.
Heart failure patients on captopril therapy should be cautioned against rapid increases in physical activity.
Patients should be informed that captopril and hydrochlorothiazide tablets should be taken one hour before meals (see DOSAGE AND ADMINISTRATION).

Non-melanoma Skin Cancer

Instruct patients taking hydrochlorothiazide to protect skin from the sun and undergo regular skin cancer screening.

Pregnancy

Female patients of childbearing age should be told about the consequences of second- and third-trimester exposure to ACE inhibitors, and they should also be told that these consequences do not appear to have resulted from intrauterine ACE-inhibitor exposure that has been limited to the first trimester. These patients should be asked to report pregnancies to their physicians as soon as possible.

Laboratory Tests

Serum electrolyte levels should be regularly monitored (see WARNINGS: Captopril and Hydrochlorothiazide; PRECAUTIONS: General: Hydrochlorothiazide).

Drug Interactions:

Captopril: Hypotension—Patients On Diuretic Therapy: Patients on diuretics and especially those in whom diuretic therapy was recently instituted, as well as those on severe dietary salt restrictions or dialysis, may occasionally experience a precipitous reduction of blood pressure usually within the first hour after receiving the initial dose of captopril.

The possibility of hypotensive effects with captopril can be minimized by either discontinuing the diuretic or increasing the salt intake approximately one week prior to initiation of treatment with captopril or initiating therapy with small doses (6.25 or 12.5 mg). Alternatively, provide medical supervision for at least one hour after the initial dose. If hypotension occurs, the patient should be placed in a supine position and, if necessary, receive an intravenous infusion of normal saline. This transient hypotensive response is not a contraindication to further doses which can be given without difficulty once the blood pressure has increased after volume expansion.

Agents Having Vasodilator Activity: Data on the effect of concomitant use of other vasodilators in patients receiving captopril for heart failure are not available; therefore, nitroglycerin or other nitrates (as used for management of angina) or other drugs having vasodilator activity should, if possible, be discontinued before starting captopril. If resumed during captopril therapy, such agents should be administered cautiously, and perhaps at lower dosage.

Agents Causing Renin Release: Captopril’s effect will be augmented by antihypertensive agents that cause renin release. For example, diuretics (e.g., thiazides) may activate the renin-angiotensin-aldosterone system.

Agents Affecting Sympathetic Activity: The sympathetic nervous system may be especially important in supporting blood pressure in patients receiving captopril alone or with diuretics. Therefore, agents affecting sympathetic activity (e.g., ganglionic blocking agents or adrenergic neuron blocking agents) should be used with caution. Beta-adrenergic blocking drugs add some further antihypertensive effect to captopril, but the overall response is less than additive.

Agents Increasing Serum Potassium: Since captopril decreases aldosterone production, elevation of serum potassium may occur. Potassium-sparing diuretics such as spironolactone, triamterene, or amiloride, or potassium supplements, should be given only for documented hypokalemia, and then with caution, since they may lead to a significant increase of serum potassium. Salt substitutes containing potassium should also be used with caution.

Gold: Nitritoid reactions (symptoms include facial flushing, nausea, vomiting and hypotension) have been reported rarely in patients on therapy with injectable gold (sodium aurothiomalate) and concomitant ACE inhibitor therapy including captopril and hydrochlorothiazide tablets.

Inhibitors of Endogenous Prostaglandin Synthesis: It has been reported that indomethacin may reduce the antihypertensive effect of captopril, especially in cases of low renin hypertension. Other non-steroidal anti-inflammatory agents (e.g., aspirin) may also have this effect.

Lithium: Increased serum lithium levels and symptoms of lithium toxicity have been reported in patients receiving concomitant lithium and ACE inhibitor therapy. These drugs should be coadministered with caution and frequent monitoring of serum lithium levels is recommended.
If a diuretic is also used, it may increase the risk of lithium toxicity (see PRECAUTIONS: Drug Interactions: Hydrochlorothiazide: Lithium).
Hydrochlorothiazide: When administered concurrently the following drugs may interact with thiazide diuretics:

Alcohol, Barbiturates, or Narcotics: potentiation of orthostatic hypotension may occur.

Amphotericin B, Corticosteroids, or Corticotropin (ACTH): may intensify electrolyte imbalance, particularly hypokalemia. Monitor potassium levels; use potassium replacements if necessary.

Anticoagulants (Oral): dosage adjustments of anticoagulant medication may be necessary since hydrochlorothiazide may decrease their effects.

Antigout Medications: dosage adjustments of antigout medication may be necessary since hydrochlorothiazide may raise the level of blood uric acid.

Other Antihypertensive Medications (e.g., Ganglionic or Peripheral Adrenergic Blocking Agents): dosage adjustments may be necessary since hydrochlorothiazide may potentiate their effects.

Antidiabetic Drugs (Oral Agents and Insulin): since thiazides may elevate blood glucose levels, dosage adjustments of antidiabetic agents may be necessary.

Calcium Salts: Increased serum calcium levels due to decreased excretion may occur. If calcium must be prescribed, monitor serum calcium levels and adjust calcium dosage accordingly.

Cardiac Glycosides: enhanced possibility of digitalis toxicity associated with hypokalemia. Monitor potassium levels (see PRECAUTIONS: Drug Interactions: Captopril).

Cholestyramine and Colestipol Resins: Absorption of hydrochlorothiazide is impaired in the presence of anionic exchange resins. Single doses of either cholestyramine or colestipol resins bind the hydrochlorothiazide and reduce its absorption from the gastrointestinal tract by up to 85 and 43 percent, respectively.

Diazoxide: enhanced hyperglycemic, hyperuricemic, and antihypertensive effects. Be cognizant of possible interaction; monitor blood glucose and serum uric acid levels.

Lithium: diuretic agents reduce the renal clearance of lithium and increase the risk of lithium toxicity. These drugs should be coadministered with caution and frequent monitoring of serum lithium levels is recommended (see PRECAUTIONS: Drug Interactions: Captopril: Lithium).

MAO Inhibitors: dosage adjustments of one or both agents may be necessary since hypotensive effects are enhanced.

Nondepolarizing Muscle Relaxants, Preanesthetics and Anesthetics Used in Surgery (e.g., Tubocurarine Chloride and Gallamine Triethiodide): effects of these agents may be potentiated; dosage adjustments may be required. Monitor and correct any fluid and electrolyte imbalances prior to surgery if feasible.

Non-steroidal Anti-inflammatory Agents: in some patients, the administration of a non-steroidal anti-inflammatory agent can reduce the diuretic, natriuretic, and antihypertensive effect of loop, potassium-sparing or thiazide diuretics. Therefore, when hydrochlorothiazide and non-steroidal anti-inflammatory agents are used concomitantly, the patient should be observed closely to determine if the desired effect of the diuretic is obtained.

Methenamine: possible decreased effectiveness due to alkalinization of the urine.

Pressor Amines (e.g., Norepinephrine): decreased arterial responsiveness, but not sufficient to preclude effectiveness of the pressor agent for therapeutic use. Use caution in patients taking both medications who undergo surgery. Administer preanesthetic and anesthetic agents in reduced dosage, and if possible, discontinue hydrochlorothiazide therapy one week prior to surgery.

Probenecid or Sulfinpyrazone: increased dosage of these agents may be necessary since hydrochlorothiazide may have hyperuricemic effects.

Drug/Laboratory Test Interactions

Captopril: Captopril may cause a false-positive urine test for acetone.
Hydrochlorothiazide: Hydrochlorothiazide may cause diagnostic interference of the bentiromide test.

Carcinogenesis, Mutagenesis, Impairment of Fertility

Carcinogenicity and fertility studies have not been conducted with captopril and hydrochlorothiazide tablets, however, in animals they have been conducted with the individual components as noted below. Mutagenecity studies indicate that captopril in a 2:1 combination with hydrochlorothiazide was not mutagenic or clastogenic, with or without metabolic activation, in the following in vitro assays: 1) Ames reverse-mutation in Salmonella; 2) forward mutation study in Saccharomyces pombe; 3) mitotic gene conversion test in Saccharomyces cerevisiae; and 4) sister-chromatid-exchange study in human lymphocytes.
In a cytogenetics study using human lymphocytes, there were no increases in chromosomal abnormalities without metabolic activation, nor with metabolic activation at 28 hours post-treatment. A statistically significant increase was found at 22 hours with metabolic activation at the three concentrations tested (captopril/hydrochlorothiazide in a 2:1 combination at 5, 25, 50 mcg/mL total weight); however, there was no dose response, and the difference is probably attributable to the unusual absence of any abnormalities in the negative-control cultures in this test.
In an oral micronucleus study in mice, the captopril/hydrochlorothiazide combination (2:1 mixture at 2500 mg/kg total weight) was not genotoxic.
Captopril: Two-year studies with doses of 50 to 1350 mg/kg/day in mice and rats failed to show any evidence of carcinogenic potential. Studies in rats have revealed no impairment of fertility.
Hydrochlorothiazide: Two-year feeding studies in mice and rats conducted under the auspices of the National Toxicology Program (NTP) uncovered no evidence of a carcinogenic potential of hydrochlorothiazide in female mice (at doses of up to approximately 600 mg/kg/day) or in male and female rats (at doses of up to approximately 100 mg/kg/day). The NTP, however, found equivocal evidence for hepatocarcinogenicity in male mice.
Hydrochlorothiazide was not genotoxic in in vitro assays using strains TA 98, TA 100, TA 1535, TA 1537 and TA 1538 of Salmonella typhimurium (Ames assay) and in the Chinese Hamster Ovary (CHO) test for chromosomal aberrations, or in vivo assays using mouse germinal cell chromosomes, Chinese hamster bone marrow chromosomes, and the Drosophilia sex linked recessive lethal trait gene. Positive test results were obtained only in the in vitro CHO Sister Chromatid Exchange (clastogenicity) and in the Mouse Lymphoma Cell (mutagenicity) assays, using concentrations of hydrochlorothiazide from 43 to 1300 mcg/mL, and in the Aspergillus nidulans non-disjunction assay at an unspecified concentration.
Hydrochlorothiazide had no adverse effects on the fertility of mice and rats of either sex in studies wherein these species were exposed, via their diet, to doses of up to 100 and 4 mg/kg, respectively, prior to conception and throughout gestation.

Animal Toxicology

Captopril: Chronic oral toxicity studies were conducted in rats (2 years), dogs (47 weeks; 1 year), mice (2 years), and monkeys (1 year). Significant drug-related toxicity included effects on hematopoiesis, renal toxicity, erosion/ulceration of the stomach, and variation of retinal blood vessels.
Reductions in hemoglobin and/or hematocrit values were seen in mice, rats, and monkeys at doses 50 to 150 times the maximum recommended human dose (MRHD). Anemia, leukopenia, thrombocytopenia, and bone marrow suppression occurred in dogs at doses 8 to 30 times MRHD. The reductions in hemoglobin and hematocrit values in rats and mice were only significant at 1 year and returned to normal with continued dosing by the end of the study. Marked anemia was seen at all dose levels (8 to 30 times MRHD) in dogs, whereas moderate to marked leukopenia was noted only at 15 and 30 times MRHD and thrombocytopenia at 30 times MRHD. The anemia could be reversed upon discontinuation of dosing. Bone marrow suppression occurred to a varying degree, being associated only with dogs that died or were sacrificed in a moribund condition in the 1 year study. However, in the 47-week study at a dose 30 times MRHD, bone marrow suppression was found to be reversible upon continued drug administration.

Captopril caused hyperplasia of the juxtaglomerular apparatus of the kidneys at doses 7 to 200 times the MRHD in rats and mice, at 20 to 60 times MRHD in monkeys, and at 30 times the MRHD in dogs.

Gastric erosions/ulcerations were increased in incidence at 20 and 200 times MRHD in male rats and at 30 and 65 times MRHD in dogs and monkeys, respectively. Rabbits developed gastric and intestinal ulcers when given oral doses approximately 30 times MRHD for only five to seven days.

In the two-year rat study, irreversible and progressive variations in the caliber of retinal vessels (focal sacculations and constrictions) occurred at all dose levels (7 to 200 times MRHD) in a dose-related fashion. The effect was first observed in the 88th week of dosing, with a progressively increased incidence thereafter, even after cessation of dosing.

Pregnancy Categories C (first trimester) and D (second and third trimesters): See WARNINGS: Captopril: Fetal/Neonatal Morbidity and Mortality.

Pregnancy: Nonteratogenic Effects: Hydrochlorothiazide: Thiazides cross the placental barrier and appear in cord blood. The use of thiazides in pregnant women requires that the anticipated benefit be weighed against possible hazards to the fetus. These hazards include fetal or neonatal jaundice, thrombocytopenia, and possibly other adverse reactions which have occurred in the adult.

Nursing Mothers

Both captopril and hydrochlorothiazide are excreted in human milk. Because of the potential for serious adverse reactions in nursing infants from both drugs, a decision should be made whether to discontinue nursing or to discontinue therapy taking into account the importance of captopril and hydrochlorothiazide to the mother. (See PRECAUTIONS: Pediatric Use.)

Pediatric Use

Safety and effectiveness in pediatric patients have not been established. There is limited experience reported in the literature with the use of captopril in the pediatric population; dosage, on a weight basis, was generally reported to be comparable to or less than that used in adults.

Infants, especially newborns, may be more susceptible to the adverse hemodynamic effects of captopril. Excessive, prolonged and un-predictable decreases in blood pressure and associated complications, including oliguria and seizures, have been reported.

Captopril and hydrochlorothiazide should be used in pediatric patients only if other measures for controlling blood pressure have not been effective.

ADVERSE REACTIONS

Captopril: Reported incidences are based on clinical trials involving approximately 7000 patients.

Renal: About one of 100 patients developed proteinuria (see WARNINGS).
Each of the following has been reported in approximately 1 to 2 of 1000 patients and are of uncertain relationship to drug use: renal insufficiency, renal failure, nephrotic syndrome, polyuria, oliguria, and urinary frequency.

Hematologic: Neutropenia/agranulocytosis has occurred (see WARNINGS). Cases of anemia, thrombocytopenia, and pancytopenia have been reported.

Dermatologic: Rash, often with pruritus, and sometimes with fever, arthralgia, and eosinophilia, occurred in about 4 to 7 (depending on renal status and dose) of 100 patients, usually during the first four weeks of therapy. It is usually maculopapular, and rarely urticarial. The rash is usually mild and disappears within a few days of dosage reduction, short-term treatment with an antihistaminic agent, and/or discontinuing therapy; remission may occur even if captopril is continued. Pruritus, without rash, occurs in about 2 of 100 patients. Between 7 and 10 percent of patients with skin rash have shown eosinophilia and/or positive ANA titers. A reversible associated pemphigoid-like lesion, and photosensitivity, have also been reported.
Flushing or pallor has been reported in 2 to 5 of 1000 patients.

Cardiovascular: Hypotension may occur; see WARNINGS and PRECAUTIONS (Drug Interactions) for discussion of hypotension with captopril therapy.
Tachycardia, chest pain, and palpitations have each been observed in approximately 1 of 100 patients.
Angina pectoris, myocardial infarction, Raynaud’s syndrome, and congestive heart failure have each occurred in 2 to 3 of 1000 patients.
Dysgeusia: Approximately 2 to 4 (depending on renal status and dose) of 100 patients developed a diminution or loss of taste perception. Taste impairment is reversible and usually self-limited (2 to 3 months) even with continued drug administration. Weight loss may be associated with the loss of taste.
Angioedema: Angioedema involving the extremities, face, lips, mucous membranes, tongue, glottis or larynx has been reported in approximately one in 1000 patients. Angioedema involving the upper airways has caused fatal airway obstruction. (See WARNINGS: Captopril: Head and Neck Angioedema and Intestinal Angioedemaand PRECAUTIONS: Information for Patients).
Cough: Cough has been reported in 0.5 to 2% of patients treated with captopril in clinical trials (see PRECAUTIONS: General: Captopril: Cough).
The following have been reported in about 0.5 to 2 percent of patients but did not appear at increased frequency compared to placebo or other treatments used in controlled trials: gastric irritation, abdominal pain, nausea, vomiting, diarrhea, anorexia, constipation, aphthous ulcers, peptic ulcer, dizziness, headache, malaise, fatigue, insomnia, dry mouth, dyspnea, alopecia, paresthesias.
Other clinical adverse effects reported since the drug was marketed are listed below by body system. In this setting, an incidence or causal relationship cannot be accurately determined.
Body as a Whole: Anaphylactoid reactions (see WARNINGS: Captopril: Anaphylactoid and Possibly Related Reactions and PRECAUTIONS: Hemodialysis).
General: asthenia, gynecomastia.
Cardiovascular: cardiac arrest, cerebrovascular accident/insufficiency, rhythm disturbances, orthostatic hypotension, syncope.
Dermatologic: bullous pemphigus, erythema multiforme (including Stevens-Johnson syndrome), exfoliative dermatitis.
Gastrointestinal: pancreatitis, glossitis, dyspepsia.
Hematologic: anemia, including aplastic and hemolytic.
Hepatobiliary: jaundice, hepatitis, including rare cases of necrosis, cholestasis.
Metabolic: symptomatic hyponatremia.
Musculoskeletal: myalgia, myasthenia.
Nervous/Psychiatric: ataxia, confusion, depression, nervousness, somnolence.
Respiratory: bronchospasm, eosinophilic pneumonitis, rhinitis.
Special Senses: blurred vision.
Urogenital: impotence.
As with other ACE inhibitors, a syndrome has been reported which may include: fever, myalgia, arthralgia, interstitial nephritis, vasculitis, rash or other dermatologic manifestations, eosinophilia and an elevated ESR.
Fetal/Neonatal Morbidity and Mortality: See WARNINGS: Captopril: Fetal/Neonatal Morbidity and Mortality.

Hydrochlorothiazide: Gastrointestinal System: anorexia, gastric irritation, nausea, vomiting, cramping, diarrhea, constipation, jaundice (intrahepatic cholestatic jaundice), pancreatitis, and sialadenitis.
Central Nervous System: dizziness, vertigo, paresthesias, headache, and xanthopsia.
Hematologic: leukopenia, agranulocytosis, thrombocytopenia, aplastic anemia, and hemolytic anemia.
Cardiovascular: orthostatic hypotension.
Hypersensitivity: purpura, photosensitivity, rash, urticaria, necrotizing angiitis (vasculitis; cutaneous vasculitis), fever, respiratory distress including pneumonitis, and anaphylactic reactions.
Other: hyperglycemia, glycosuria, hyperuricemia, muscle spasm, weakness, restlessness, and transient blurred vision.
Whenever adverse reactions are moderate or severe, thiazide dosage should be reduced or therapy withdrawn.
Altered Laboratory Findings: Serum Electrolytes: Hyperkalemia: small increases in serum potassium, especially in patients with renal impairment (see PRECAUTIONS: Captopril).
Hyponatremia: particularly in patients receiving a low sodium diet or concomitant diuretics.
BUN/Serum Creatinine: Transient elevations of BUN or serum creatinine especially in volume or salt depleted patients or those with renovascular hypertension may occur. Rapid reduction of longstanding or markedly elevated blood pressure can result in decreases in the glomerular filtration rate and, in turn, lead to increases in BUN or serum creatinine.
Hematologic: A positive ANA has been reported.
Liver Function Tests: Elevations of liver transaminases, alkaline phosphatase, and serum bilirubin have occurred.
Postmarketing Experience: Non-melanoma Skin Cancer: Hydrochlorothiazide is associated with an increased risk of non-melanoma skin cancer. In a study conducted in the Sentinel System, increased risk was predominantly for squamous cell carcinoma (SCC) and in white patients taking large cumulative doses. The increased risk for SCC in the overall population was approximately 1 additional case per 16,000 patients per year, and for white patients taking a cumulative dose of ≥ 50,000 mg the risk increase was approximately 1 additional SCC case for every 6,700 patients per year.
To report SUSPECTED ADVERSE REACTIONS, contact Rising Pharma Holdings, Inc. at 1-844- 874-7464 or FDA at 1-800-FDA-1088 or www.fda.gov/medwatch.

OVERDOSAGE

Captopril: Correction of hypotension would be of primary concern. Volume expansion with an intravenous infusion of normal saline is the treatment of choice for restoration of blood pressure.
While captopril may be removed from the adult circulation by hemodialysis, there is inadequate data concerning the effectiveness of hemodialysis for removing it from the circulation of neonates or children. Peritoneal dialysis is not effective for removing captopril; there is no information concerning exchange transfusion for removing captopril from the general circulation.
Hydrochlorothiazide: In addition to the expected diuresis, overdosage of thiazides may produce varying degrees of lethargy which may progress to coma within a few hours, with minimal depression of respiration and cardiovascular function and without evidence of serum electrolyte changes or dehydration. The mechanism of thiazide-induced CNS depression is unknown. Gastrointestinal irritation and hypermotility may occur. Transitory increase in BUN has been reported, and serum electrolyte changes may occur, especially in patients with impaired renal function.
In addition to gastric lavage and supportive therapy for stupor or coma, symptomatic treatment of gastrointestinal effects may be needed. The degree to which hydrochlorothiazide is removed by hemodialysis has not been clearly established. Measures as required to maintain hydration, electrolyte balance, respiration, and cardiovascular and renal function should be instituted.

DOSAGE & ADMINISTRATION

DOSAGE MUST BE INDIVIDUALIZED ACCORDING TO PATIENT'S RESPONSE.
Captopril and hydrochlorothiazide tablets may be substituted for the previously titrated individual components.
Alternatively, therapy may be instituted with a single tablet of captopril and hydrochlorothiazide 25 mg/15 mg taken once daily. For patients insufficiently responsive to the initial dose, additional captopril or hydrochlorothiazide may be added as individual components or by using captopril and hydrochlorothiazide tablets 50 mg/15 mg, 25 mg/25 mg or 50 mg/25 mg, or divided doses may be used.
Because the full effect of a given dose may not be attained for 6 to 8 weeks, dosage adjustments should generally be made at 6 week intervals, unless the clinical situation demands more rapid adjustment.
In general, daily doses of captopril should not exceed 150 mg and of hydrochlorothiazide should not exceed 50 mg.
Captopril and hydrochlorothiazide tablets should be taken one hour before meals.
Dosage Adjustment in Renal Impairment: Because captopril and hydrochlorothiazide are excreted primarily by the kidneys, excretion rates are reduced in patients with impaired renal function. These patients will take longer to reach steady-state captopril levels and will reach higher steady-state levels for a given daily dose than patients with normal renal function. Therefore, these patients may respond to smaller or less frequent doses of captopril and hydrochlorothiazide.
After the desired therapeutic effect has been achieved, the dose intervals should be increased or the total daily dose reduced until the minimal effective dose is achieved. When concomitant diuretic therapy is required in patients with severe renal impairment, a loop diuretic (e.g., furosemide), rather than a thiazide diuretic is preferred for use with captopril; therefore, for patients with severe renal dysfunction the captopril-hydrochlorothiazide combination tablet is not usually recommended. (See WARNINGS: Captopril: Anaphylactoid Reactions During Membrane Exposureand PRECAUTIONS: Hemodialysis).

HOW SUPPLIED

Captopril and Hydrochlorothiazide Tablets, USP are available containing 25 mg or 50 mg of captopril, USP with 15 mg or 25 mg of hydrochlorothiazide, USP providing the following available combinations: 25 mg/15 mg, 25 mg/25 mg, 50 mg/15 mg or 50 mg/25 mg.

The 25 mg/15 mg tablets are supplied as a white, round, biconvex tablet debossed with ‘R over 27’ on one side of the tablet and quadrisect scored on the other side. They are available as follows:
Bottles of 90 tablets - NDC 16571-827-09

The 25 mg/25 mg tablets are supplied as a peach, round, biconvex tablet debossed with ‘R over 28’ on one side of the tablet and quadrisect scored on the other side. They are available as follows:
Bottles of 90 tablets - NDC 16571-828-09

The 50 mg/15 mg tablets are supplied as a white, capsule-shaped, biconvex tablet debossed with ‘R’ to the left of the partial score and ‘29’ to the right of the partial score on one side of the tablet and partially scored on the other side. They are available as follows:
Bottles of 90 tablets - NDC 16571-829-09

The 50 mg/25 mg tablets are supplied as a peach, capsule-shaped, biconvex tablet debossed with R to the left of the partial score and 30 to the right of the partial score on one side of the tablet and partially scored on the other side. They are available as follows:
Bottles of 90 tablets - NDC 16571-830-09

Dispense in a tight, light-resistant container as defined in the USP using a child-resistant closure.
Keep container tightly closed.

Store at 20° to 25°C (68° to 77°F). [See USP Controlled Room Temperature.]
Protect from moisture.

Manufactured for:
Rising Pharma Holdings, Inc.
East Brunswick, NJ 08816

Issued: 12/2022
200640
PIR83001-00

PACKAGE LABEL.PRINCIPAL DISPLAY PANEL

25 mg/15 mg: NDC: 16571-827-09

Captopril and Hydrochlorothiazide Tablets, USP 25 mg/ 15 mg

Rx only 90 Tablets

25 mg/25 mg: NDC: 16571-828-09

Captopril and Hydrochlorothiazide Tablets, USP 25 mg/ 25 mg

Rx only 90 Tablets

50 mg/15 mg: NDC: 16571-829-09

Captopril and Hydrochlorothiazide Tablets, USP 50 mg/ 15 mg

Rx only 90 Tablets

50 mg/25 mg: NDC: 16571-830-09

Captopril and Hydrochlorothiazide Tablets, USP 50 mg/ 25 mg

Rx only 90 Tablets